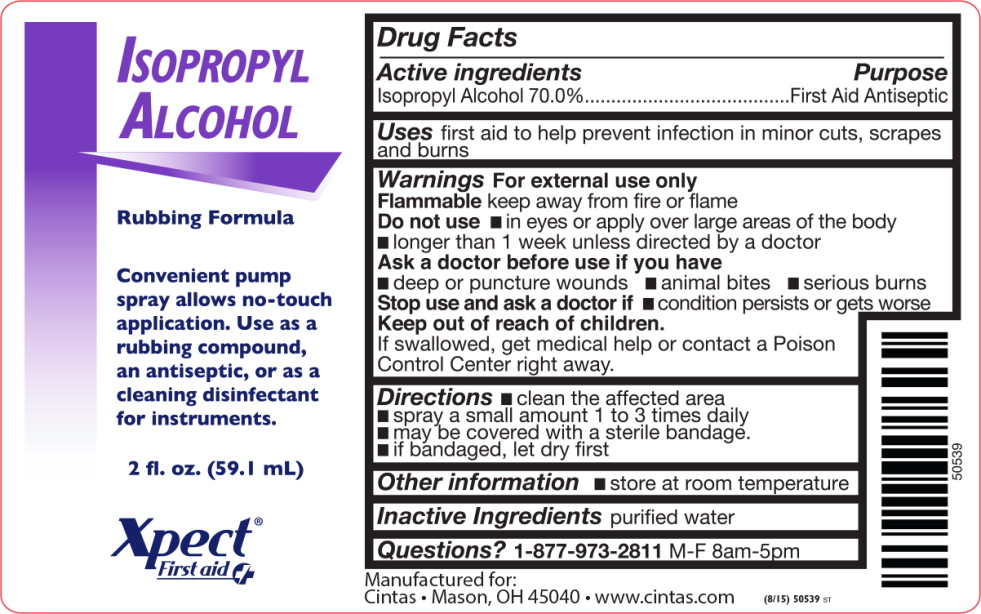 DRUG LABEL: Isopropyl Alcohol
NDC: 68421-5500 | Form: SPRAY
Manufacturer: Cintas First Aid & Safety
Category: otc | Type: HUMAN OTC DRUG LABEL
Date: 20150903

ACTIVE INGREDIENTS: isopropyl alcohol 550.2 g/1 L
INACTIVE INGREDIENTS: water

Isopropyl Alcohol spray

Drug Facts

Active Ingredient

Isopropyl Alcohol 70.0%

Purpose

First Aid Antiseptic

Uses

First aid to help prevent infection in minor cuts, scrapes & burns

Warnings

For external use only

Flammable, keep away from fire or flame

Do not use

- in eyes or apply over large areas of the body
- longer than 1 week unless directed by a doctor

Ask a doctor before use if you have

- deep or puncture wounds, animal bites, or serious burns

Stop use and consult doctor if

- the condition persists or gets worse

Keep out of reach of children. If swallowed, get medical help or contact a Poison Control Center right away.

Directions

- clean the affected area
- spray a small amount of this product on the area 1 to 3 times daily
- may be covered with a sterile bandage
- if bandaged, let dry first

Other information

- store at room temperature

Inactive ingredients

purified water

Questions or Comments?

1-800-327-2704

Manufactured for: Respond Industries and
American First Aid, Mason, OH 45040

Principal Display Panel - Bottle Label

Isopropyl
Alcohol

Rubbing Formula

Convenient pump
spray allows no-touch
application. Use as a
rubbing compound,
an antiseptic, or as a
cleaning disinfectant
for instruments.

2 fl. oz. (59.1 mL)

Xpect®
First aid